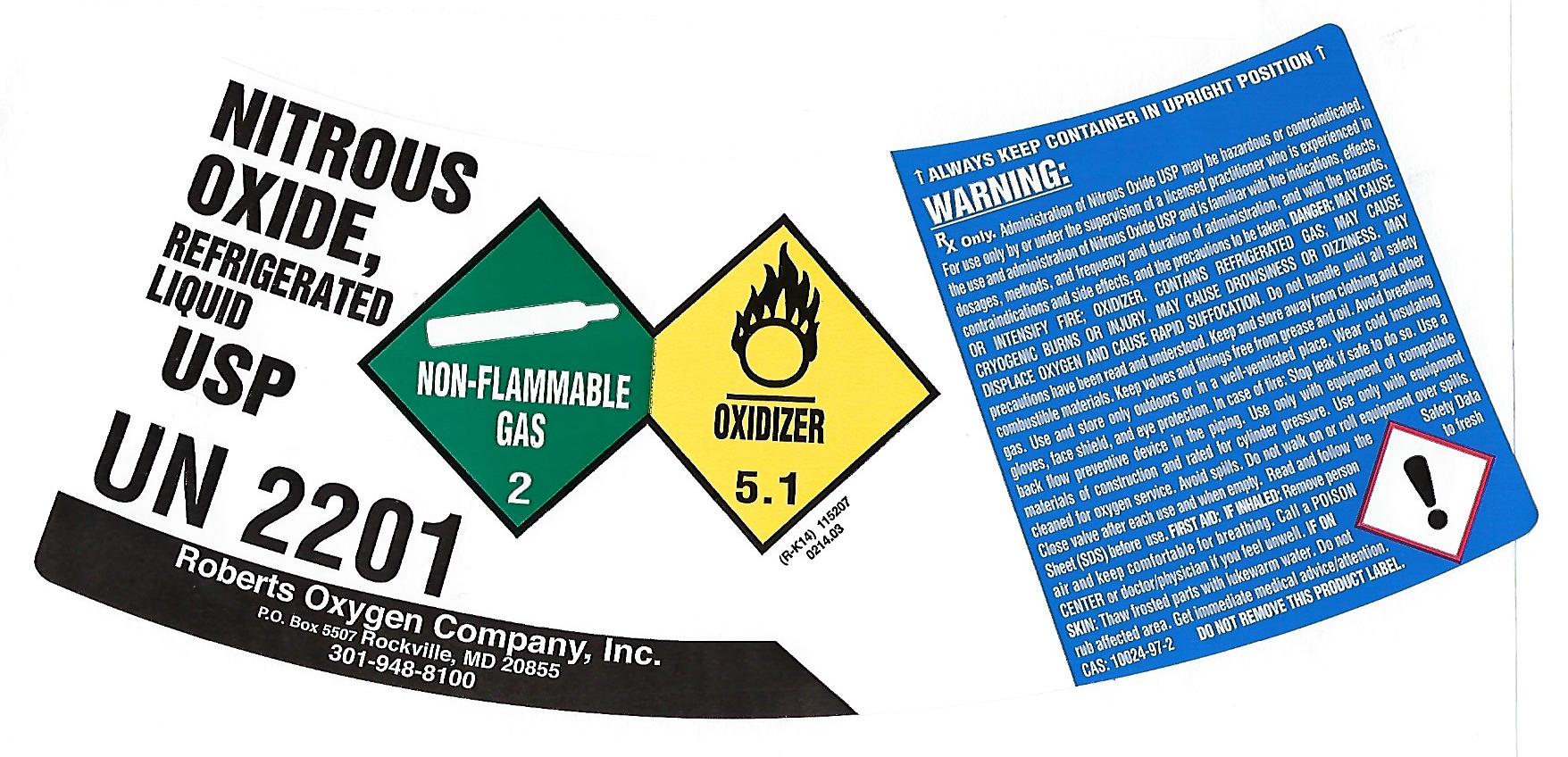 DRUG LABEL: Nitrous Oxide
NDC: 46123-007 | Form: GAS
Manufacturer: Roberts Oxygen Company, Inc.
Category: prescription | Type: HUMAN PRESCRIPTION DRUG LABEL
Date: 20251117

ACTIVE INGREDIENTS: NITROUS OXIDE 990 mL/1 L

Nitrous Oxide-007

PACKAGE LABEL

NITROUS
OXIDE,
REFRIGERATED
LIQUID
USP
UN2201
NON-FLAMMABLE GAS 2
OXIDIZER 5.1
Roberts Oxygen Company, Inc
P.O. BOX 5507 Rockville, MD 20855
301-948-8100
↑ALWAYS KEEP CONTAINER IN UPRIGHT POSITION↑
WARNING:
Rx Only. Administration of Nitrous Oxide USP may be hazardous or contraindicated. For use only by or under the supervision of a licensed practitioner who is experienced in the use and administration of Nitrous Oxide USP and is familiar with the indications, effects, dosages, methods, and frequency and duration of administration, and the hazards, contraindications and side effects and the precautions to be taken. DANGER: MAY CAUSE OR INTENSIFY FIRE; OXIDIZER. CONTAINS REFRIGERATED GAS; MAY CAUSE CRYOGENIC BURNS OR INJURY. MAY CAUSE DROWSINESS OR DIZZINESS. MAY DISPLACE OXYGEN AND CAUSE RAPID SUFFOCATION. Do not handle until all safety precautions have been read and understood. Keep and store away from clothing and other combustible materials. Keep valves and fitting free from grease and oil. Avoid breathing gas. Use and store only outdoors or in a well-ventilated place. Wear cold insulating gloves, face shield, and eye protection. In case of fire: Stop leak if safe to do so. Use a back flow preventative device in the piping. Use only with equipment of compatible materials of construction and rated for cylinder pressure. Use only with equipment cleaned for oxygen service. Avoid spills. Do not walk or roll equipment over spills. Close valve after each use and when empty. Read and follow the Safety Data Sheet (SDS) before use. FIRST AID: IF INHALED: Remove person to fresh air and keep comfortable for breathing. Call a POISON CENTER or doctor/physician if you feel unwell. IF ON SKIN: Thaw frosted parts with lukewarm water. Do not rub affected area. Get immediate medical advice/attention.
CAS: 10024-97-2 DO NOT REMOVE THIS PRODUCT LABEL.